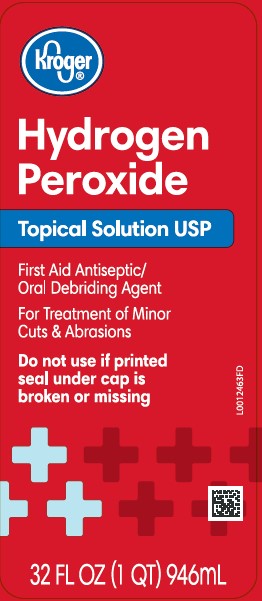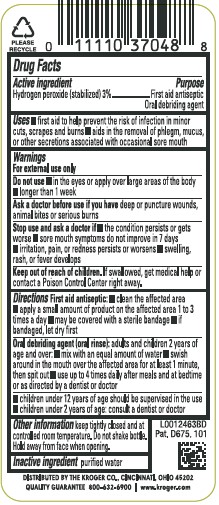 DRUG LABEL: Hydrogen Peroxide
NDC: 30142-871 | Form: SOLUTION
Manufacturer: The Kroger Co.
Category: otc | Type: HUMAN OTC DRUG LABEL
Date: 20260227

ACTIVE INGREDIENTS: HYDROGEN PEROXIDE 30 mg/1 mL
INACTIVE INGREDIENTS: WATER

Kroger 871.0001/871AA
Hydrogen Peroxide

Active ingredient

Hydrogen peroxide (stablized) 3%

Purpose

First Aid Antiseptic

Oral debriding agent

Uses

- first aid to help prevent the risk of infection in minor cuts, scrapes and burns
- aids in the removal of phlegm, mucus, or other secretions associated with occasional sore mouth

Warnings

For external use only

Do not use

- in the eyes or apply over large areas of the the body
- longer than one week

Ask a doctor before use if you have

deep or puncture wounds, animal bites or serious burns

Stop use and ask a doctor if

- the condition persists or gets worse
- sore mouth symptoms do not improve in 7 days
- irritation, pain or redness persists or worsens
- swelling, rash, or fever develops

Keep out of reach of children.

If swallowed, get medical help or contact a Poison Control Center right away.

Directions

First Aid Antiseptic:

- clean the affected area
- apply a small amount of product on the affected area 1 to 3 times a day
- may be covered with a sterile bandage
- if bandaged, let dry first

Oral debriding agent (oral rinse): adults and children over 2 years of age:

- mix with an equal amount of water
- swish around in the mouth over the affected area for at least 1 minute, then spit out
- use up to 4 times daily after meals and at bedtime

- children under 12 years of age should be supervised in the use
- children 2 years of age: consult a dentist, doctor

Other information

keep tightly closed and at controlled room temperature. Do not shake bottle. Hold away from face when opening.

Inactive ingredient

purified water

ADVERSE REACTION

DISTRIBUTED BY THE KROGER CO., CINCINNATI, OHIO 45202

QUALITY GUARANTEE 800-632-6900 www.kroger.com

Pat. D675, 101

principal display panel

Kroger®

Hydrogen Peroxide

Topical Solution USP

First Aid Antiseptic / Oral Debriding Agent

For Treatment of Minor Cuts & Abrasions

Do not use if printed seal under cap is broken or missing

32 FL OZ (1 QT) 946 mL